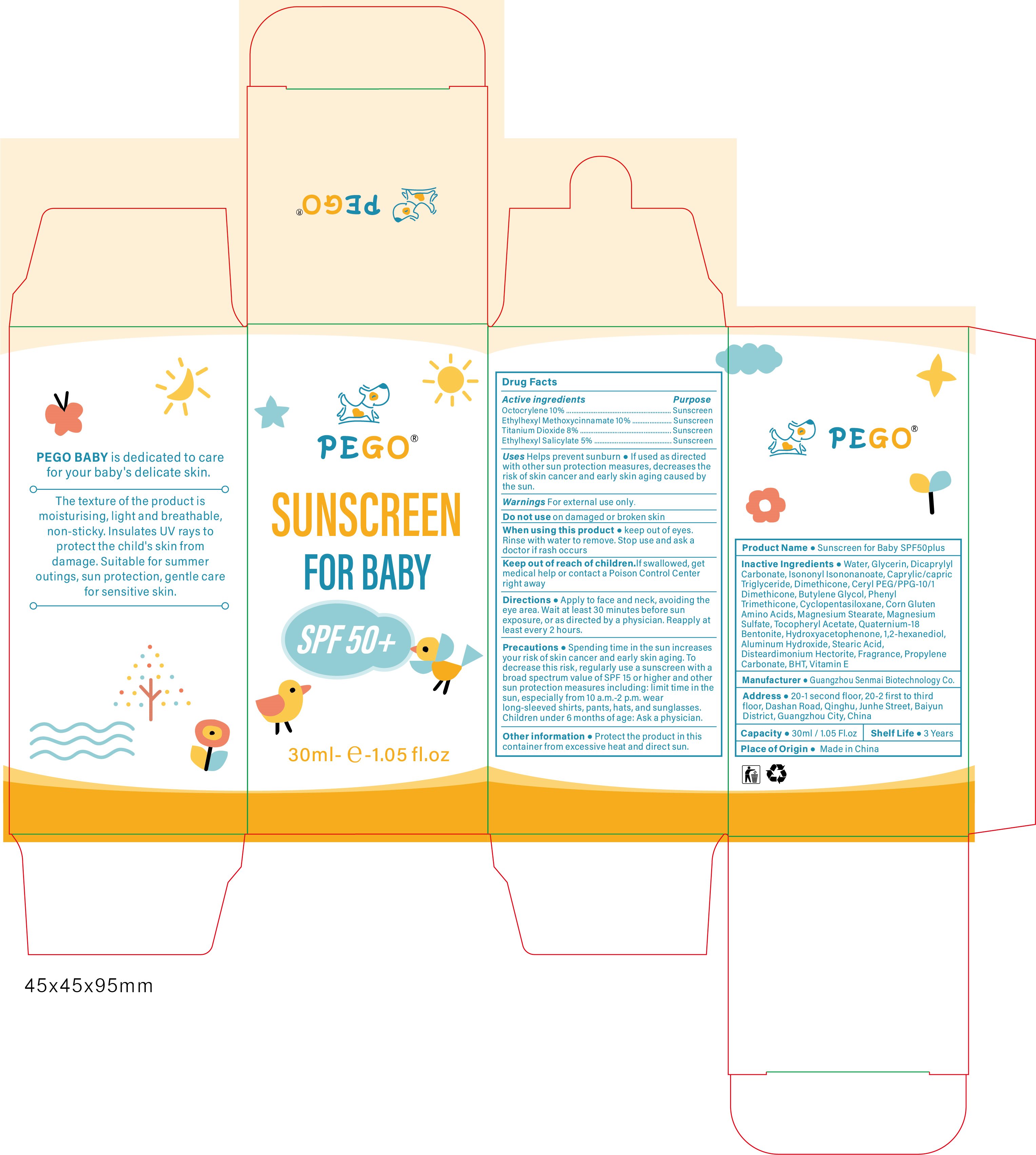 DRUG LABEL: Sunscreen for baby SPF50plus
NDC: 84509-001 | Form: LOTION
Manufacturer: Guangzhou Senmai Biotechnology Co., Ltd.
Category: otc | Type: HUMAN OTC DRUG LABEL
Date: 20250108

ACTIVE INGREDIENTS: OCTOCRYLENE 3000 mg/30 mL; TITANIUM DIOXIDE 2400 mg/30 mL; OCTINOXATE 3000 mg/30 mL; OCTISALATE 1500 mg/30 mL
INACTIVE INGREDIENTS: ISONONYL ISONONANOATE; DIMETHICONE; PHENYL TRIMETHICONE; PROPYLENE CARBONATE; WATER; TRICAPRILIN; CETYL PEG/PPG-10/1 DIMETHICONE (HLB 5); BUTYLENE GLYCOL; CYCLOMETHICONE 5; HYDROXYACETOPHENONE; BENTOQUATAM; 1,2-HEXANEDIOL; BUTYLATED HYDROXYTOLUENE; .ALPHA.-TOCOPHEROL; GLYCERIN; .ALPHA.-TOCOPHEROL ACETATE; ALUMINUM HYDROXIDE; DICAPRYLYL CARBONATE; AMINO ACIDS, CORN GLUTEN; MAGNESIUM SULFATE, UNSPECIFIED; STEARIC ACID; DISTEARDIMONIUM HECTORITE; FRAGRANCE 13576; MAGNESIUM STEARATE

Active Ingredients

Octocrylene 10%

Ethylhexyl methoxycinnamate 10%

Titanium Dioxide 8%

Ethylhexyl salicylate 5%

Purpose

Sunscreen

Uses

Helps prevent sunburn

If used as directed with other sun protection measures, decreases the risk of skin cancer and early skin aging caused by the sun.

Warnings

For external use only.

Do not use

on damaged or broken skin

When using this product

Keep out of eyes. Rinse with water to remove. Stop and ask a doctor if rash occurs.

Keep out of reach of children.

If swallowed, get medical help or contact a Poison Control Center right away

Directions

Apply to face and neck, avoiding the eye area. Wait at least 30 minutes before sun exposure, or as directed by a physician. Reapply at least every 2 hours.

Precautions

Spending time in the sun increases your risk of skin cancer and early skin aging. To decrease this risk, regularly use a sunscreen with a broad spectrum value of SPF 15 or higher and other sun protection measures including: limit time in the sun, especially from 10 a.m.-2 p.m.wearlong-sleeved shirts, pants, hats, and sunglasses. Children under 6 months of age: Ask a physician,

Other information

Protect the product in this container from excessive heat and direct sun.

Product Name

Sunscreen for Baby SPF50plus

Inactive Ingredients

Water, Glycerin, Dicaprylyl Carbonate, lsononyl lsononanoate, Caprylic/capric Triglyceride, Dimethicone, Ceryl PEG/PPG-10/1 Dimethicone, Butylene Glycol, Phenyl Trimethicone, Cyclopentasiloxane, Corn Gluten Amino Acids, Magnesium Stearate, Magnesium Sulfate, Tocopheryl Acetate, Quaternium-18 Bentonite, Hydroxyacetophenone, 1,2-hexanediol, Aluminum Hydroxide, Stearic Acid, Disteardimonium Hectorite, Fragrance, PropyleneCarbonate, BHT, Vitamin E

Manufacturer

Guangzhou Senmai Biotechnology Co.

Address

20-1second floor, 20-2 first to third floor,Dashan Road,Qinghu,Junhe Street, Baiyun district, Guangzhou City, China

Capacity

30ml/1.05 Fl.oz

Shelf Life

3 Years

Place of Origin

Made in China